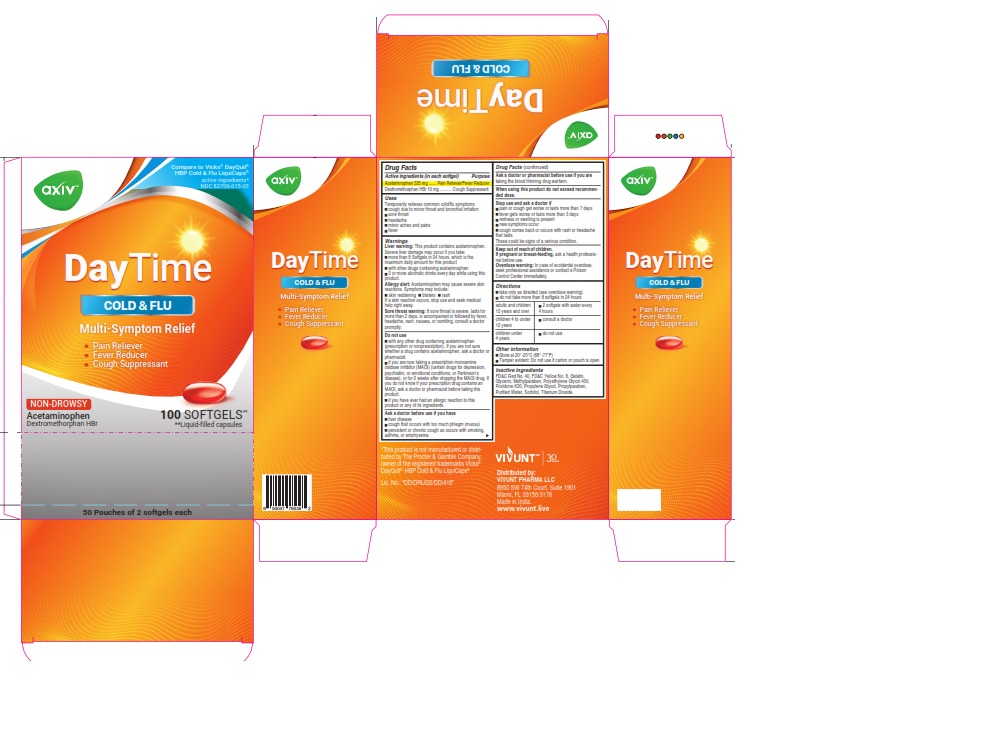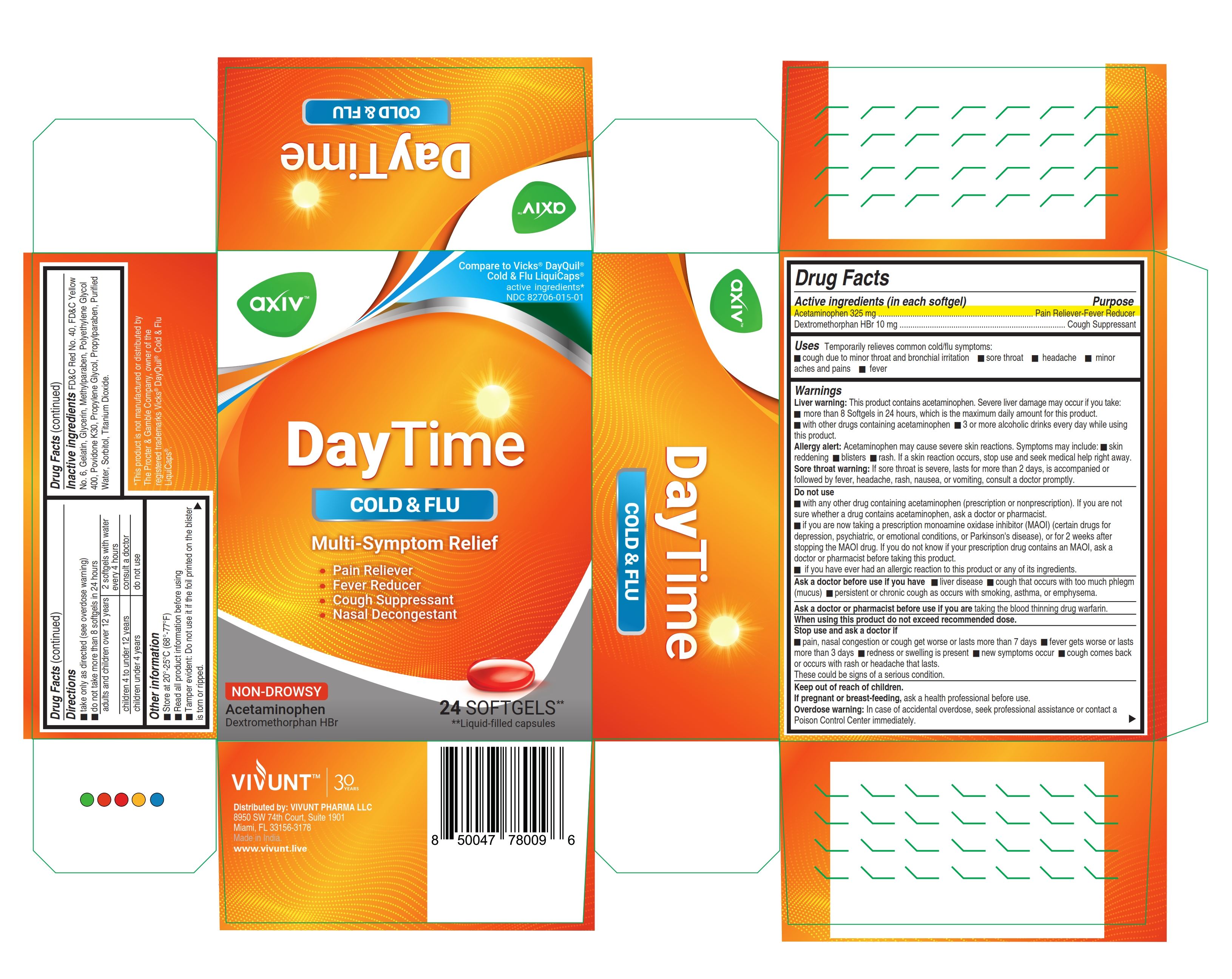 DRUG LABEL: AXIV DayTime
NDC: 82706-015 | Form: CAPSULE, LIQUID FILLED
Manufacturer: VIVUNT PHARMA LLC
Category: otc | Type: HUMAN OTC DRUG LABEL
Date: 20250212

ACTIVE INGREDIENTS: ACETAMINOPHEN 325 mg/1 1; DEXTROMETHORPHAN HYDROBROMIDE 10 mg/1 1
INACTIVE INGREDIENTS: METHYLPARABEN; GLYCERIN; FD&C YELLOW NO. 6; FD&C RED NO. 40; GELATIN; POLYETHYLENE GLYCOL 400; POVIDONE K30; PROPYLENE GLYCOL; WATER; PROPYLPARABEN; SORBITOL; TITANIUM DIOXIDE

AXIV - DayTime Cold & Flu

Drug Facts

ACTIVE INGREDIENT

Active ingredients (in each softgel) | Purpose
Acetaminophen 325 mg | Pain Reliever/Fever Reducer
Dextromethorphan HBr 10 mg | Cough Suppressant

Uses

Temporarily relieves common cold/flu symptoms:

- cough due to minor throat and bronchial irritation
- sore throat
- headache
- minor aches and pains
- fever

Warnings

Liver warning

This product contains acetaminophen. Severe liver damage may occur if you take

- more than 8 Softgels in 24 hours, which is the maximum daily amount for this product
- with other drugs containing acetaminophen
- 3 or more alcoholic drinks every day while using this product

Allergy alert

Acetaminophen may cause severe skin reactions. Symptoms may include:

- skin reddening
- blisters
- rash

If a skin reaction occurs, stop use and seek medical help right away

Sore throat warning

If sore throat is severe, lasts for more than 2 days, is accompanied or followed by fever, headache, rash, nausea, or vomiting, consult a doctor promptly.

Do not use

- with any other drug containing acetaminophen (prescription or nonprescription). If you are not sure whether a drug contains acetaminophen, ask a doctor or pharmacist.
- if you are now taking a prescription monoamine oxidase inhibitor (MAOI) (certain drugs for depression, psychiatric, or emotional conditions, or Parkinson's disease), or for 2 weeks after stopping the MAOI drug. If you do not know if your prescription drug contains an MAOI, ask a doctor or pharmacist before taking this product.
- if you have ever had an allergic reaction to this product or any of its ingredients

Ask a doctor before use if you have

- liver disease
- cough that occurs with too much phlegm (mucus)
- persistent or chronic cough as occurs with smoking, asthma, or emphysema

When using this product

do not exceed recommended dose

Stop use and ask a doctor if

- pain or cough gets worse or lasts more than 7 days
- fever gets worse or lasts more than 3 days
- redness or swelling is present
- new symptoms occur
- cough comes back or occurs with rash or headache that lasts.

These could be signs of a serious condition

Keep out of reach of children

If pregnant or breast-feeding

ask a health professional before use.

Overdose warning

In case of accidental overdose, seek professional assistance or contact a Poison Control Center immediately.

Directions

- Take only as directed (see overdose warning)
- Do not take more than 8 softgels in 24 hours.

adults and children 12 years and over | 2 softgels with water every 4 hours
children 4 to under 12 years | consult a doctor
children under 4 years | do not use

Other information

- Store at 20° - 25 °C (68 °- 77 °F)
- Read all product information before using
- Tamper evident: Do not use if carton is open or blister unit is broken.
- Tamper evident: Do not use if carton or pouch is open

Inactive ingredients

FD&C Red No. 40, FD&C Yellow No. 6, Gelatin, Glycerin, Methylparaben, Polyethylene Glycol 400, Povidone K30, Propylene Glycol, Propylparaben, Purified Water, Sorbitol, Titanium Dioxide

Distributed by:

VIVUNT PHARMA LLC
8950 SW 74th. Court. Suite 1901

Miami, Florida, 33156-3178

Made in India

www.vivunt.live

PRINCIPAL DISPLAY PANEL AXIV DayTime Carton 24 AXIV DayTime Carton 100

Compare to

VICKS ® DayQuil®

Cold&Flu LiquiCaps®

active ingredients*

NDC 82706-015-01

AXIV - DayTime

COLD&FLU

Multi-Symptom Relief

- Pain Reliever
- Fever Reducer
- Cough Suppressant
- Nasal Decongestant

Non-Drowsy

Acetaminophen, Dextromethorphan HBr

24 SOFTGELS** **Liquid-filled capsules

*This product is not manufactured or distributed by

The Procter &Gamble Company, owner of the registered trademarks Vicks® DayQuil®

and LiquiCaps®.

Compare to

VICKS ® DayQuil®

Cold&Flu LiquiCaps®

active ingredients*

NDC 82706-015-03

AXIV - DayTime

COLD&FLU

Multi-Symptom Relief

Pain Reliever
Fever Reducer
Cough Suppressant

Non-Drowsy

Acetaminophen, Dextromethorphan HBr

100 SOFTGELS** **Liquid-filled capsules

*This product is not manufactured or distributed by

The Procter &Gamble Company, owner of the registered trademarks Vicks® DayQuil®

and LiquiCaps®.